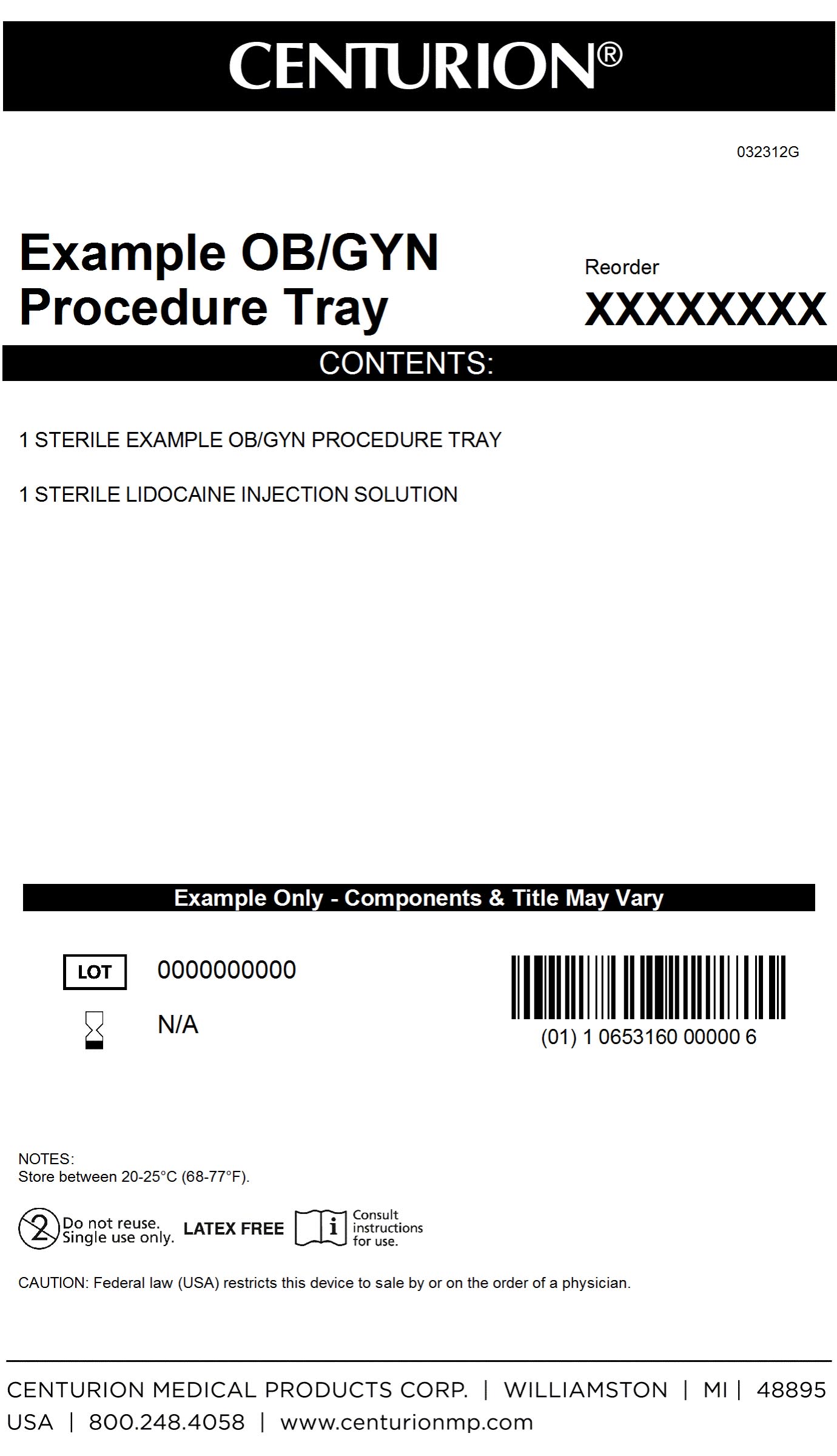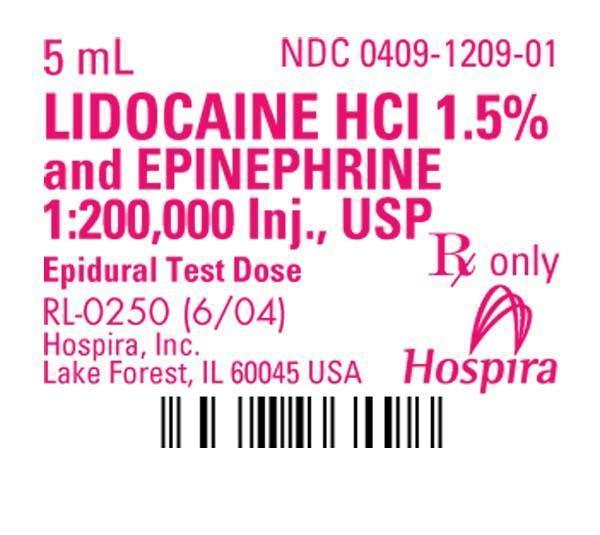 DRUG LABEL: OB GYN Procedure Kit
NDC: 24840-1711 | Form: KIT | Route: EPIDURAL
Manufacturer: Centurion Medical Products
Category: other | Type: MEDICAL DEVICE
Date: 20120924

ACTIVE INGREDIENTS: LIDOCAINE HYDROCHLORIDE ANHYDROUS 15 mg/1 mL; EPINEPHRINE 5 ug/1 mL
INACTIVE INGREDIENTS: SODIUM CHLORIDE 6.5 mg/1 mL; SODIUM METABISULFITE 0.5 mg/1 mL; ANHYDROUS CITRIC ACID 0.2 mg/1 mL; SODIUM HYDROXIDE; HYDROCHLORIC ACID; WATER

OBGYN Procedure Kit

DESCRIPTION

Lidocaine Hydrochloride and Epinephrine Injection, USP is a sterile, nonpyrogenic solution of lidocaine hydrochloride and epinephrine in water for injection for parenteral administration. Sodium metabisulfate 0.5 mg/ml and citric acid, anhydrous 0.2 mg/ml added as stabilizers. May contain sodium hydroxide and/or hydrochloric acid to adjust pH; pH is 4.5 (3.3 to 5.5). Single dose ampuls and vial contain no bacteriostat or antimicrobial agent. Discard unused portion. Lidocaine is a local anesthetic of the amide type.

PACKAGE LABEL

MM